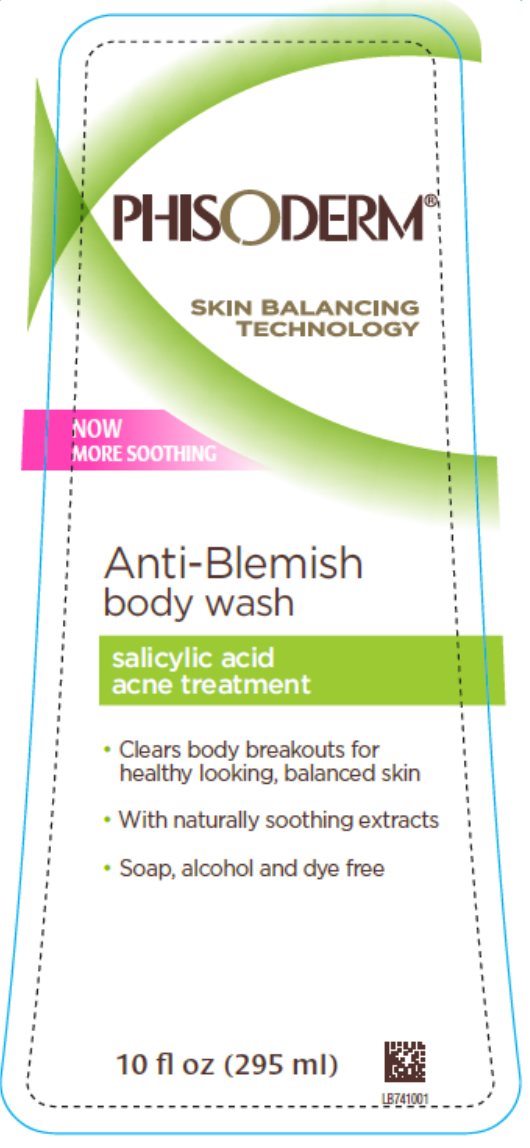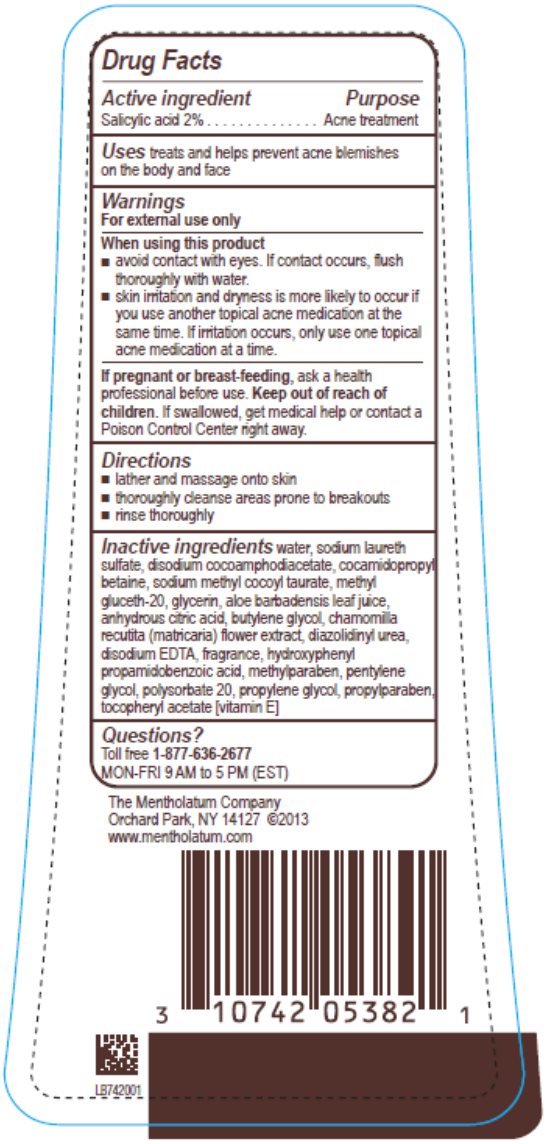 DRUG LABEL: Phisoderm Anti Blemish Body Wash
NDC: 10742-8451 | Form: LIQUID
Manufacturer: The Mentholatum Company
Category: otc | Type: HUMAN OTC DRUG LABEL
Date: 20241217

ACTIVE INGREDIENTS: SALICYLIC ACID 20 mg/1 mL
INACTIVE INGREDIENTS: WATER; SODIUM LAURETH-3 SULFATE; DISODIUM COCOAMPHODIACETATE; COCAMIDOPROPYL BETAINE; SODIUM METHYL COCOYL TAURATE; METHYL GLUCETH-20; GLYCERIN; ALOE VERA LEAF; ANHYDROUS CITRIC ACID; 1,2-BUTANEDIOL; CHAMOMILE; DIAZOLIDINYL UREA; EDETATE DISODIUM; HYDROXYPHENYL PROPAMIDOBENZOIC ACID; METHYLPARABEN; PENTYLENE GLYCOL; POLYSORBATE 20; PROPYLENE GLYCOL; PROPYLPARABEN; .ALPHA.-TOCOPHEROL ACETATE

Drug Facts - pHisoderm Anti Blemish Body Wash

Active ingredient

Salicylic acid 2%

Purpose

Acne Treatment

Uses

treats and helps prevent acne blemishes on the body and face

Warnings

For external use only

When using this product

- avoid contact with eyes. If contact occurs, flush thoroughly with water.
- skin irritation and dryness is more likely to occur if you use another topical acne medication at the same time. If irritation occurs, only use one topical acne medication at a time.

If pregnant or breast-feeding,

ask a health professional before use.

Keep out of reach of children.

If swallowed, get medical help or contact a Poison Control Center right away.

Directions

- lather and massage onto skin
- thoroughly cleanse areas prone to breakouts
- rinse thoroughly

Inactive ingredients

water, sodium laureth sulfate, disodium cocoamphodiacetate, cocamidopropyl betaine, sodium methyl cocoyl taurate, methyl gluceth-20, glycerin, aloe barbadensis leaf juice, anhydrous citric acid, butylene glycol, chamomilla recutita (matricaria) flower extract, diazolidinyl urea, disodium EDTA, fragrance, hydroxyphenyl propamidobenzoic acid, methylparaben, pentylene glycol, polysorbate 20, propylene glycol, propylparaben, tocopheryl acetate [vitamin E]

Questions?

Toll free 1-877-636-2677 MON-FRI 9 AM to 5 PM (EST)